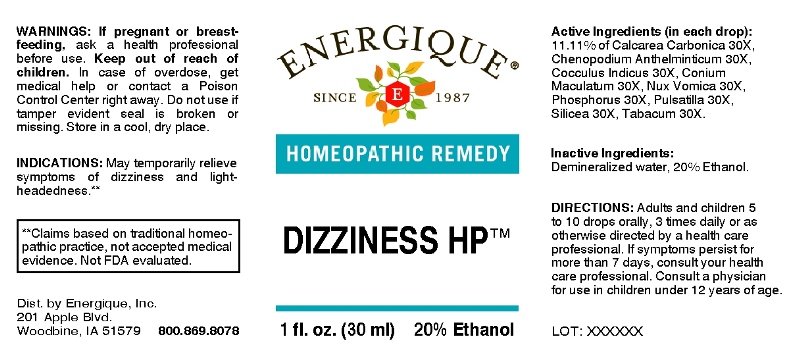 DRUG LABEL: Dizziness
NDC: 44911-0187 | Form: LIQUID
Manufacturer: Energique, Inc.
Category: homeopathic | Type: HUMAN OTC DRUG LABEL
Date: 20251119

ACTIVE INGREDIENTS: OYSTER SHELL CALCIUM CARBONATE, CRUDE 30 [hp_X]/1 mL; DYSPHANIA AMBROSIOIDES 30 [hp_X]/1 mL; ANAMIRTA COCCULUS SEED 30 [hp_X]/1 mL; CONIUM MACULATUM FLOWERING TOP 30 [hp_X]/1 mL; STRYCHNOS NUX-VOMICA SEED 30 [hp_X]/1 mL; PHOSPHORUS 30 [hp_X]/1 mL; PULSATILLA PRATENSIS WHOLE 30 [hp_X]/1 mL; SILICON DIOXIDE 30 [hp_X]/1 mL; TOBACCO LEAF 30 [hp_X]/1 mL
INACTIVE INGREDIENTS: WATER; ALCOHOL

DRUG FACTS:

ACTIVE INGREDIENTS:

(in each drop): 11.11% of Calcarea Carbonica 30X, Chenopodium Anthelminticum 30X, Cocculus Indicus 30X, Conium Maculatum 30X, Nux Vomica 30X, Phosphorus 30X, Pulsatilla (Pratensis)30X, Silicea 30X, Tabacum 30X.

INDICATIONS:

May temporarily relieve symptoms of dizziness and light-headedness.**

**Claims based on traditional homeopathic practice, not accepted medical evidence. Not FDA evaluated.

WARNINGS:

If pregnant or breast-feeding, ask a health professional before use.

Keep out of reach of children. In case of overdose, get medical help or contact a Poison Control Center right away.

Do not use if tamper evident seal is broken or missing. Store in a cool, dry place.

Keep out of reach of children. In case of overdose, get medical help or contact a Poison Control Center right away.

DIRECTIONS:

Adults and children 5 to 10 drops orally, 1 time daily or as otherwise directed by a health care professional. If symptoms persist, consult your health care professional.

Consult a physician for use in children under 12 years of age.

INDICATIONS:

May temporarily relieve symptoms of dizziness and light-headedness.**

**Claims based on traditional homeopathic practice, not accepted medical evidence. Not FDA evaluated.

INACTIVE INGREDIENTS:

Demineralized water, 20% Ethanol.

QUESTIONS:

Dist. by Energique, Inc.

201 Apple Blvd

Woodbine, IA 51579 800.869.8078

PACKAGE LABEL DISPLAY:

ENERGIQUE

SINCE 1987

HOMEOPATHIC REMEDY

DIZZINESS HP

1 fl. oz. (30 ml)